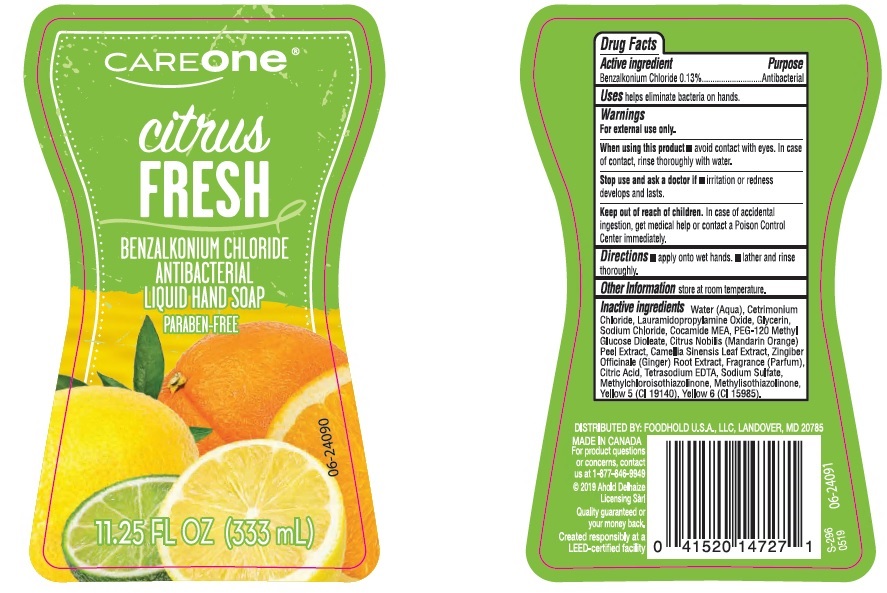 DRUG LABEL: CareOne Citrus Fresh Antibacterial Hand
NDC: 41520-303 | Form: SOAP
Manufacturer: American Sales Company
Category: otc | Type: HUMAN OTC DRUG LABEL
Date: 20190719

ACTIVE INGREDIENTS: BENZALKONIUM CHLORIDE 1.3 mg/1 mL
INACTIVE INGREDIENTS: WATER; CETRIMONIUM CHLORIDE; LAURAMIDOPROPYLAMINE OXIDE; GLYCERIN; SODIUM CHLORIDE; COCO MONOETHANOLAMIDE; PEG-120 METHYL GLUCOSE DIOLEATE; TANGERINE PEEL; GREEN TEA LEAF; GINGER; CITRIC ACID MONOHYDRATE; EDETATE SODIUM; SODIUM SULFATE; METHYLCHLOROISOTHIAZOLINONE; METHYLISOTHIAZOLINONE; FD&C YELLOW NO. 5; FD&C YELLOW NO. 6

Drug Facts

Active ingredient

Benzalkonium Chloride 0.13%

Purpose

Antibacterial

Uses

helps eliminate bacteria on hands.

Warnings

For external use only.

When using this product

- avoid contact with eyes. In case of contact, rinse thoroughly with water.

Stop use and ask a doctor if

- irritation or redness develops and lasts.

Keep out of reach of children.

In case of accidental ingestion, get medical help or contact a Poison Control Center immediately.

Directions

- apply onto wet hands.
- lather and rinse thoroughly.

Other information

store at room temperature.

Inactive ingredients

Water (Aqua), Cetrimonium Chloride, Lauramidopropylamine Oxide, Glycerin, Sodium Chloride, Cocamide MEA, PEG-120 Methyl Glucose Dioleate, Citrus Nobilis (Mandarin Orange) Peel Extract, Camellia Sinensis Leaf Extract, Zingiber Officinale (Ginger) Root Extract, Fragrance (Parfum), Citric Acid, Tetrasodium EDTA, Sodium Sulfate, Methylchloroisothiazolinone, Methylisothiazolinone, Yellow 5 (CI 19140), Yellow 6 (CI 15985).